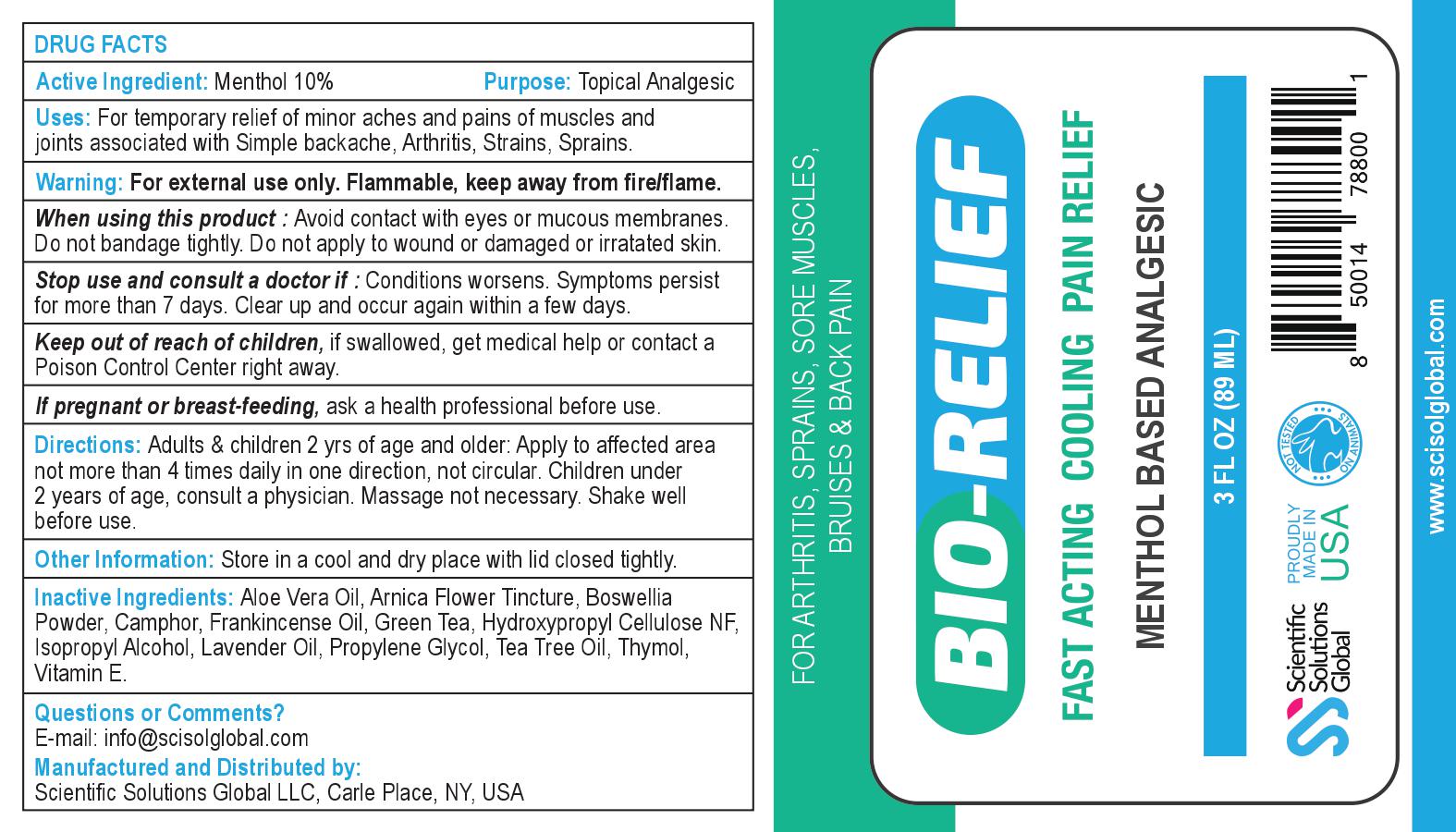 DRUG LABEL: Bio-Relief
NDC: 71718-200 | Form: GEL
Manufacturer: Scientific Solutions Global LLC
Category: otc | Type: HUMAN OTC DRUG LABEL
Date: 20200211

ACTIVE INGREDIENTS: MENTHOL, UNSPECIFIED FORM 8.9 g/89 mL
INACTIVE INGREDIENTS: ISOPROPYL ALCOHOL; CAMPHOR (SYNTHETIC); PROPYLENE GLYCOL; LAVENDER OIL; HYDROXYPROPYL CELLULOSE, UNSPECIFIED; ARNICA MONTANA; ALPHA-TOCOPHEROL; TEA TREE OIL; ALOE VERA LEAF; THYMOL

PACKAGE LABEL

ACTIVE INGREDIENT

Menthol 10%

PURPOSE

Topical Analgesic

INDICATIONS AND USAGE

For temporary relief of minor aches and pains of muscles and joints associated with • simple backache • arthritis • strains• bruises • sprains

WARNINGS

For external use only. Flammable, keep away from fire/flame.

Keep out of reach of children, if swallowed, get medical help or contact a Poison Control Center right away.

DOSAGE AND ADMINISTRATION

Adults & children 2 yrs of age and older: Apply to affected area not more than 4 times daily in one direction, not circular. Children under 2 years of age, consult a physician. Massage not necessary. Shake well before use.

INACTIVE INGREDIENT

Aloe Vera Oil, Arnica Flower Tincture, Boswellia Powder, Camphor, Frankincense Oil, Green Tea, Hydroxypropyl Cellulose NF, Isopropyl Alcohol, Lavender Oil, Propylene Glycol, Tea Tree Oil, Thymol, Vitamin E.

OTHER SAFETY INFORMATION

Store in a cool and dry place with lid closed tightly.

Questions or Comments? E-mail: info@scisolglobal.com Manufactured and Distributed by: Scientific Solutions Global LLC, Carle Place, NY, USA